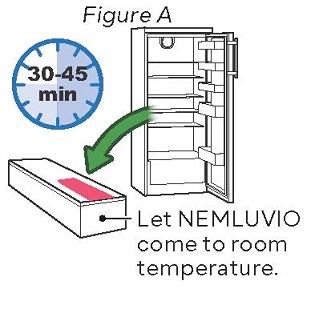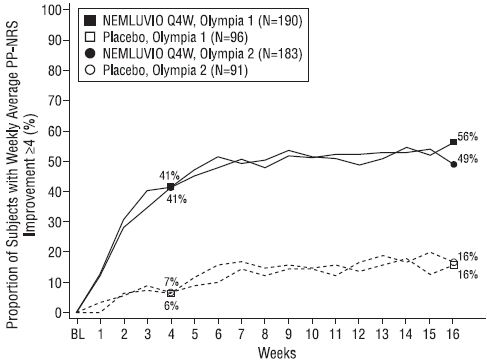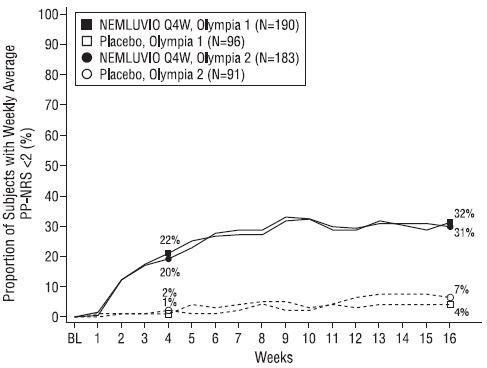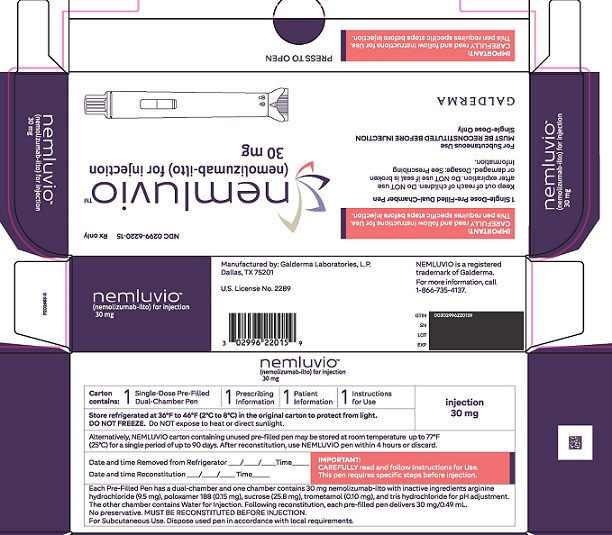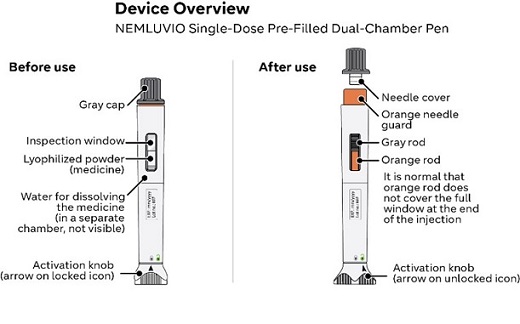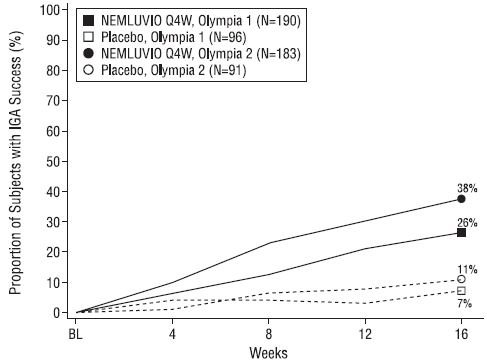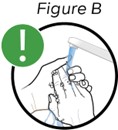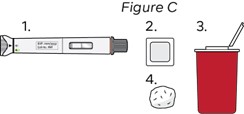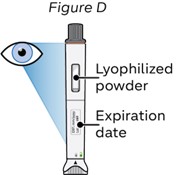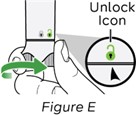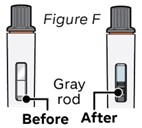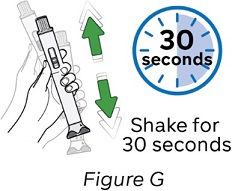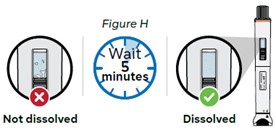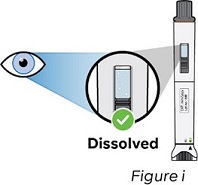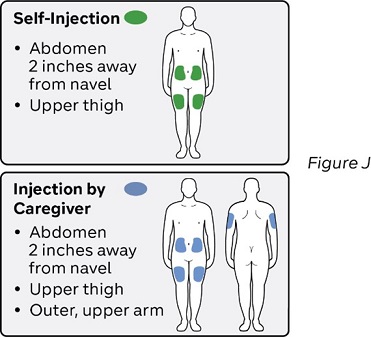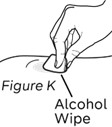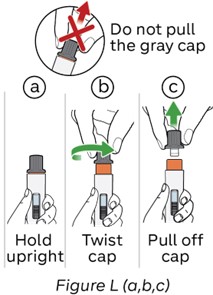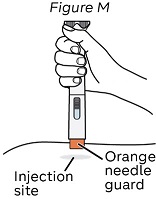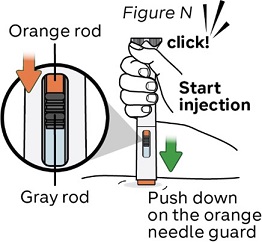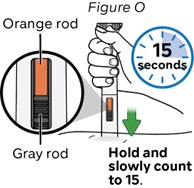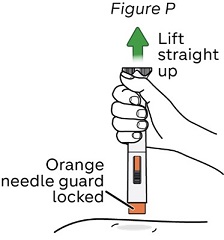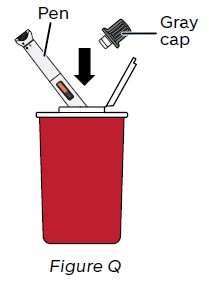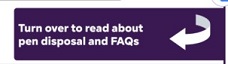 DRUG LABEL: NEMLUVIO
NDC: 0299-6220 | Form: INJECTION, POWDER, LYOPHILIZED, FOR SOLUTION
Manufacturer: Galderma Laboratories, L.P.
Category: prescription | Type: HUMAN PRESCRIPTION DRUG LABEL
Date: 20250626

ACTIVE INGREDIENTS: Nemolizumab 30 mg/100 mg
INACTIVE INGREDIENTS: Sucrose; Tromethamine; Tromethamine Hydrochloride; Poloxamer 188; Water

HIGHLIGHTS OF PRESCRIBING INFORMATION

These highlights do not include all the information needed to use NEMLUVIO safely and effectively. See full prescribing information for NEMLUVIO.
NEMLUVIO® (nemolizumab-ilto) for injection, for subcutaneous use
Initial U.S. Approval: 2024

1 INDICATIONS AND USAGE

NEMLUVIO is an interleukin-31 receptor antagonist indicated for:
Prurigo Nodularis
The treatment of adults with prurigo nodularis. (1.1)
Atopic Dermatitis
The treatment of adults and pediatric patients 12 years of age and older with moderate-to-severe atopic dermatitis in combination with topical corticosteroids and/or calcineurin inhibitors when the disease is not adequately controlled with topical prescription therapies. (1.2)

RECENT MAJOR CHANGES

Indications and Usage, Atopic Dermatitis (1.2) | 06/2025
Dosage and Administration, Atopic Dermatitis (2.3) | 06/2025

2 DOSAGE AND ADMINISTRATION

Complete all age-appropriate vaccinations as recommended by current immunization guidelines prior to treatment with NEMLUVIO. (2.1)

Prurigo Nodularis:

- Adult Patients Weighing Less Than 90kg: The recommended subcutaneous dosage is an initial dose of 60 mg (two 30 mg injections), followed by 30 mg given every 4 weeks. (2.2)
- Adult Patients Weighing 90kg or More: The recommended subcutaneous dosage is an initial dose of 60 mg (two 30 mg injections), followed by 60 mg given every 4 weeks. (2.2)

Atopic Dermatitis:

- The recommended subcutaneous dosage is an initial dose of 60 mg (two 30 mg injections), followed by 30 mg given every 4 weeks. (2.3)
- After 16 weeks of treatment, for patients who achieve clear or almost clear skin, a dosage of 30 mg every 8 weeks is recommended. (2.3)
- Use NEMLUVIO with topical corticosteroids and/or topical calcineurin inhibitors. When the disease has sufficiently improved, discontinue use of topical therapies. (2.3)
- Administer NEMLUVIO by subcutaneous injection. (2.5)
- NEMLUVIO must be reconstituted prior to administration. (2.6)

3 DOSAGE FORMS AND STRENGTHS

For injection: single-dose, prefilled, dual-chamber pen containing 30 mg of nemolizumab-ilto lyophilized powder and diluent, water for injection. (3)

4 CONTRAINDICATIONS

Known hypersensitivity to nemolizumab-ilto or to any of the excipients in NEMLUVIO. (4)

5 WARNINGS AND PRECAUTIONS

- Hypersensitivity: Hypersensitivity reactions have been reported with NEMLUVIO use. If a clinically significant hypersensitivity reaction occurs, immediately institute appropriate therapy and discontinue NEMLUVIO. (5.1)
- Vaccinations: Avoid use of live vaccines during treatment with NEMLUVIO. (5.2)

6 ADVERSE REACTIONS

Most common adverse reactions are:

- Prurigo Nodularis (incidence ≥1%): headache, dermatitis atopic, eczema, and eczema nummular. (6.1)
- Atopic Dermatitis (incidence ≥1%): headache (including migraine), arthralgia, urticaria, and myalgia. (6.1)

To report SUSPECTED ADVERSE REACTIONS, contact Galderma Laboratories, L.P. at 1-866-735-4137 or FDA at 1-800-FDA-1088 or www.fda.gov/medwatch.

FULL PRESCRIBING INFORMATION

1 INDICATIONS AND USAGE

NEMLUVIO is indicated for the treatment of adults with prurigo nodularis.

1.2 Atopic Dermatitis

NEMLUVIO is indicated for the treatment of adults and pediatric patients 12 years of age and older with moderate-to-severe atopic dermatitis in combination with topical corticosteroids and/or calcineurin inhibitors when the disease is not adequately controlled with topical prescription therapies.

2 DOSAGE AND ADMINISTRATION

2.1 Vaccination Prior to Treatment

Complete all age-appropriate vaccinations as recommended by current immunization guidelines prior to treatment with NEMLUVIO [see Warnings and Precautions (5.2)].

2.2 Recommended Dosage for Prurigo Nodularis

Adult Patients Weighing Less Than 90 kg:
The recommended subcutaneous dosage of NEMLUVIO for adult patients weighing less than 90 kg is an initial dose of 60 mg (two 30 mg injections), followed by 30 mg given every 4 weeks.
Adult Patients Weighing 90 kg or More:
The recommended subcutaneous dosage of NEMLUVIO for adult patients weighing 90 kg or more is an initial dose of 60 mg (two 30 mg injections), followed by 60 mg given every 4 weeks.

2.3 Recommended Dosage for Atopic Dermatitis

The recommended subcutaneous dosage of NEMLUVIO in adults and pediatric patients 12 years of age and older is an initial dose of 60 mg (two 30 mg injections), followed by 30 mg given every 4 weeks.
After 16 weeks of treatment, for patients who achieve clear or almost clear skin, a subcutaneous dosage of 30 mg every 8 weeks is recommended.
Concomitant Topical Therapies:
Use NEMLUVIO with topical corticosteroids and/or topical calcineurin inhibitors. When the disease has sufficiently improved, discontinue use of topical therapies.

2.4 Missed Dose

If a dose is missed, administer the dose as soon as possible. Thereafter, resume dosing at the regular scheduled time.

2.5 Important Administration Instructions

- NEMLUVIO is administered by subcutaneous injection.
- NEMLUVIO is intended for use under the guidance of a healthcare provider. Prior to the first injection, provide patients and/or caregivers with proper training on the preparation and administration of NEMLUVIO. Patients may self-inject NEMLUVIO after receiving training on subcutaneous injection techniques. In pediatric patients 12 years of age and older, administer NEMLUVIO by or under the supervision of a trained adult or caregiver.
- For the initial dose, administer each of the two NEMLUVIO injections at different injection sites.
- Administer NEMLUVIO subcutaneously into the front upper thighs or abdomen avoiding the 2-inch (5 cm) area around the navel. NEMLUVO may be subcutaneously injected into the upper arm, but this should only be performed by a caregiver or healthcare professional.
- Alternate the injection site with each injection. Do not inject NEMLUVIO into skin that is tender, inflamed, swollen, damaged or has bruises or scars or open wounds.
- Refer to the Instructions for Use for complete administration instructions with illustrations [see Instructions for Use].

2.6 Preparation for Use of NEMLUVIO

- Before injection, remove NEMLUVIO carton from the refrigerator and allow to reach room temperature (30-45 minutes).
- Inspect NEMLUVIO visually prior to reconstitution. NEMLUVIO is supplied in a single-dose, prefilled, dual-chamber pen with white powder in one chamber and a clear diluent in the other chamber. Do not use if powder is not white, or if diluent is cloudy or contains visible particles.
- NEMLUVIO must be reconstituted prior to administration. Refer to the Instructions for Use for complete preparation instructions with illustrations [see Instructions for Use].
- Following reconstitution, each prefilled pen delivers 30 mg/0.49 mL as a clear and colorless to slightly yellow solution. Parenteral drug products should be inspected visually for particulate matter and discoloration prior to administration, whenever solution and container permit. Do not use if the reconstituted solution has discoloration or contains particles.
- Use NEMLUVIO pens within 4 hours after reconstitution. Discard unused reconstituted NEMLUVIO pens after 4 hours.
- Discard any unused portions after administration.

3 DOSAGE FORMS AND STRENGTHS

For injection: single-dose, prefilled, dual-chamber pen containing 30 mg of nemolizumab-ilto as a white lyophilized powder in one chamber and diluent, water for injection, in the other chamber.

4 CONTRAINDICATIONS

NEMLUVIO is contraindicated in patients who have known hypersensitivity to nemolizumab-ilto or to any of the excipients in NEMLUVIO [see Warnings and Precautions (5.1)].

5 WARNINGS AND PRECAUTIONS

5.1 Hypersensitivity

Hypersensitivity reactions, such as facial angioedema, have been reported with use of NEMLUVIO. NEMLUVIO is contraindicated in patients with a known hypersensitivity to nemolizumab-ilto or to any of the excipients in NEMLUVIO. If a clinically significant hypersensitivity reaction occurs, immediately institute appropriate therapy and discontinue NEMLUVIO [see Contraindications (4), Adverse Reactions (6.1)].

5.2 Vaccinations

Complete all age-appropriate vaccinations as recommended by current immunization guidelines prior to treatment with NEMLUVIO. Avoid use of live vaccines in patients during treatment with NEMLUVIO. It is unknown if administration of live vaccines during NEMLUVIO treatment will impact the safety or effectiveness of these vaccines. No data are available on the response to non-live vaccines.

6 ADVERSE REACTIONS

The following clinically significant adverse reactions are described in greater details elsewhere in the labeling:

- Hypersensitivity [see Warnings and Precautions (5.1)]

6.1 Clinical Trials Experience

Because clinical trials are conducted under widely varying conditions, adverse reaction rates observed in the clinical trials of a drug cannot be directly compared to rates in the clinical trials of another drug and may not reflect the rates observed in practice.

Prurigo Nodularis
A total of 508 adult subjects with prurigo nodularis were treated with NEMLUVIO in two placebo-controlled trials and an open label long-term extension trial. Of these, 375 subjects were exposed for at least 1 year in the drug development program for prurigo nodularis.

The safety of NEMLUVIO in adult subjects with prurigo nodularis was evaluated in two randomized, doubleblind, placebo-controlled, multicenter trials (OLYMPIA 1 and OLYMPIA 2). Subjects were treated for up to 24 weeks in OLYMPIA 1 and up to 16 weeks in OLYMPIA 2. In these 2 trials, 370 subjects were treated with subcutaneous injections of NEMLUVIO, and 186 subjects received placebo [see Clinical Studies (14.1)].

Subjects weighing less than 90 kg in the NEMLUVIO group received an initial NEMLUVIO dose of 60 mg or placebo at Week 0, followed by a NEMLUVIO dose of 30 mg or placebo every 4 weeks. Subjects weighing 90 kg or more in the NEMLUVIO group received an initial NEMLUVIO dose of 60 mg or placebo at Week 0 followed by a NEMLUVIO dose of 60 mg or placebo every 4 weeks.

During the treatment period in Trials OLYMPIA 1 and OLYMPIA 2, the proportion of subjects who discontinued treatment because of adverse reactions was 4% in the NEMLUVIO group versus 3% in the placebo group. Table 1 summarizes the adverse reactions that occurred at a rate of at least 1% in the NEMLUVIO group, and for which the rate exceeds the rate in the placebo group through Week 16.

Table 1: Adverse Reactions Occurring in ≥1% of Adult Subjects with Prurigo Nodularis in the NEMLUVIO Group and Greater than Placebo in the OLYMPIA 1 and OLYMPIA 2 Trials through Week 16.
Adverse Reaction | NEMLUVIO N= 370 n (%) | Placebo (N= 186) n (%)
Headache* | 23 (6) | 6 (3)
Dermatitis atopic | 16 (4) | 1 (0.5)
Eczema | 14 (4) | 3 (2)
Eczema nummular | 11 (3) | 0
*includes: headache and tension headache

Specific Adverse Reactions
Hypersensitivity reactions
Type 1 hypersensitivity reactions (Ig-E mediated reactions), including one report of discrete facial (peri-ocular) angioedema, were reported in subjects treated with NEMLUVIO [see Contraindications (4)].

Atopic Dermatitis
Adults and Pediatric Subjects 12 Years of Age and Older
A total of 1148 subjects, including 180 subjects 12 to 17 years of age, with moderate-to-severe atopic dermatitis were treated with NEMLUVIO for at least 1 year during the drug development program.

The safety of NEMLUVIO was evaluated in a pool of two randomized, double-blind, placebo-controlled, multicenter phase 3 trials (ARCADIA 1, ARCADIA 2). In these two trials, 1135 adult and pediatric subjects 12 years of age and older with moderate-to-severe AD were treated with subcutaneous injections of NEMLUVIO (initial dose of 60 mg, followed by 30 mg every 4 weeks), with concomitant topical corticosteroids (TCS) and/or topical calcineurin inhibitors (TCI) for up to 16 weeks (Initial Treatment Period) [see Clinical Studies (14.2)].

After the Initial Treatment Period, subjects who responded to NEMLUVIO were re-randomized to receive NEMLUVIO 30 mg every 4 weeks, NEMLUVIO 30 mg every 8 weeks, or placebo every 4 weeks for the Maintenance Treatment Period (Week 16 through Week 48) [see Clinical Studies (14.2)]. The safety population during the Maintenance Treatment Period had a mean age of 31 to 33 years (median age of 26 to 29 years) for the NEMLUVIO cohorts.

Week 0 to Week
16 In ARCADIA 1 and ARCADIA 2 trials through Week 16, the proportion of subjects who discontinued treatment because of adverse events was 2.3% in the NEMLUVIO every 4 weeks group and 2.2% in the placebo groups. Table 2 summarizes the adverse reactions that occurred at a rate of at least 1% in the NEMLUVIO group, and for which the rate exceeds the rate in the placebo group during the first 16 weeks of treatment.

Table 2: Adverse Reactions Occurring in ≥1% of Adult and Pediatric Subjects 12 Years of Age and Older with Atopic Dermatitis in the NEMLUVIO Group and Greater than in the Placebo Group in ARCADIA 1 and ARCADIA 2 Trials through Week 16
Adverse reactions | NEMLUVIO N = 1135 n (%) | Placebo N=584 n (%)
Headache (incl. migraine) | 52 (5) | 22 (4)
Arthralgia | 12 (1) | 1 (0.2)
Urticaria | 12 (1) | 2 (0.3)
Myalgia | 11 (1) | 1 (0.2)

Assessment of the safety profile of NEMLUVIO in 505 subjects up through Week 48 in the ARCADIA 1 and ARCADIA 2 trials was generally consistent with the safety profile observed at Week 16.

Specific Adverse Reactions

Hypersensitivity reactions
Type 1 hypersensitivity reactions (Ig-E mediated reactions) were reported in subjects treated with NEMLUVIO. This included occurrence of mild urticaria that did not lead to discontinuation of treatment.

Injection site reactions
The incidence of injection site reactions during the initial treatment period was reported for 1.2% of subjects treated with NEMLUVIO and 0.9% of subjects receiving placebo; during the maintenance period, the incidence was 0.6% with NEMLUVIO every 4 weeks, 0% with NEMLUVIO every 8 weeks, and 0% with placebo. None of these reactions led to discontinuation of treatment.

Herpes Zoster
During the initial treatment period, herpes zoster infections were reported in 5 subjects (0.4%) treated with NEMLUVIO (including 1 case of ophthalmic herpes zoster) and no subjects receiving placebo. Cases of herpes zoster were mild to moderate in severity and did not lead to discontinuation of treatment.

Pediatric Subjects 12 Years of Age and Older
The safety of NEMLUVIO was assessed in 176 subjects 12 to 17 years of age with moderate-to-severe atopic dermatitis enrolled in the ARCADIA 1 or ARCADIA 2 trials who received at least one dose of NEMLUVIO from Week 0 to Week 16 in the primary safety population. The safety profile of NEMLUVIO in these subjects through Week 16 was consistent with the safety profile observed in adults with atopic dermatitis.

The safety profile of NEMLUVIO in 98 subjects 12 to 17 years of age followed through Week 48 was consistent with the safety profile observed at Week 16.

8 USE IN SPECIFIC POPULATIONS

8.1 Pregnancy

Risk Summary
Available data on NEMLUVIO use in pregnant women exposed during clinical trials are insufficient to evaluate for a drug-associated risk of major birth defects, miscarriage, or other adverse maternal or fetal outcomes. In an enhanced pre- and postnatal development study in cynomolgus monkeys, when nemolizumab-ilto was administered subcutaneously during organogenesis to parturition, an increase in early postnatal death was observed at a dose 36 times the maximum recommended human dose (MRHD) for PN and 50 times for AD (see Data). The clinical significance of this nonclinical finding is unknown.
The background risk of major birth defects and miscarriage for the indicated populations are unknown. All pregnancies have a background risk of birth defects, loss, or other adverse outcomes. In the U.S. general population, the estimated background risk of major birth defects and miscarriage in clinically recognized pregnancies is 2% to 4% and 15% to 20%, respectively.

Clinical Considerations
Fetal/Neonatal Adverse Reactions
Transport of endogenous IgG antibodies across the placenta increases as pregnancy progresses, and peaks during the third trimester. Therefore, NEMLUVIO may be present in infants exposed in utero. The potential impact of infants being exposed in utero to NEMLUVIO should be considered.

Data
Animal Data
In an enhanced pre- and postnatal development study, subcutaneous doses up to 25 mg/kg of nemolizumab-ilto were administered to pregnant cynomolgus monkeys once every two weeks during organogenesis to parturition. No maternal or embryofetal toxicities were observed at doses up to 25 mg/kg (36 times the MRHD for PN and 50 times for AD, based on AUC comparison). Early postnatal death occurred in the offspring of one control monkey and 3 monkeys at 25 mg/kg (36 times the MRHD for PN and 50 times for AD, based on AUC comparison). The clinical significance of this nonclinical finding is unknown. Nemolizumab-ilto was administered subcutaneously to the offspring at doses up to 25 mg/kg (122 times the MRHD for PN and 168 times for AD, based on AUC comparison), once every 2 weeks for 6 months, starting from postnatal day 35. No adverse effects were noted in the remaining offspring.

8.2 Lactation

Risk Summary
There are no data on the presence of nemolizumab-ilto in human milk, the effects on the breastfed infant, or the effects on milk production. Nemolizumab-ilto was detected in breast milk of monkeys (see Data). Endogenous maternal IgG and monoclonal antibodies are transferred in human milk. The effects of local gastrointestinal exposure and limited systemic exposure in the breastfed infant to nemolizumab-ilto are unknown. The developmental and health benefits of breastfeeding should be considered along with the mother’s clinical need for NEMLUVIO and any potential adverse effects on the breastfed child from NEMLUVIO or from the underlying maternal condition.

Data
Nemolizumab-ilto was detected in breast milk of monkeys in the enhanced pre- and postnatal development study following subcutaneous doses up to 25 mg/kg once every two weeks during organogenesis to parturition. The mean nemolizumab-ilto concentrations in milk were approximately 0.3 – 0.5% of the maternal plasma levels from lactation day 7 to 63. The concentration of nemolizumab-ilto in animal milk does not necessarily predict the concentration of drug in human milk.

8.4 Pediatric Use

Prurigo Nodularis
The safety and effectiveness of NEMLUVIO have not been established in pediatric patients.

Atopic Dermatitis
The safety and effectiveness of NEMLUVIO for the treatment of moderate-to-severe atopic dermatitis in combination with topical corticosteroids and/or calcineurin inhibitors have been established in pediatric patients 12 years of age and older whose disease is not adequately controlled with topical prescription therapies. Use of NEMLUVIO for this indication is supported by evidence from two randomized, double-blind, placebo-controlled trials [See Adverse Reactions (6.1) and Clinical Studies (14.2)].
The safety and effectiveness of NEMLUVIO have not been established in pediatric patients younger than 12 years of age.

8.5 Geriatric Use

Prurigo Nodularis
Of the 370 subjects with prurigo nodularis exposed to NEMLUVIO in OLYMPIA 1 and OLYMPIA 2, 99 (26.8%) subjects were 65 years of age or older. The long-term safety of NEMLUVIO was assessed in 508 subjects, among which 133 (26.2%) were 65 years of age or older. Clinical trials of NEMLUVIO did not include sufficient numbers of subjects 65 years of age or older to determine whether they respond differently than younger adult subjects. [see Clinical Pharmacology (12.3)].

Atopic Dermatitis
Of the 1192 subjects with atopic dermatitis exposed to NEMLUVIO in the primary safety population, 72 (6.0%) subjects were 65 years of age or older. The long-term safety of NEMLUVIO was assessed in 78 (4.5%) subjects 65 years of age or older. Clinical studies of NEMLUVIO did not include sufficient numbers of subjects aged 65 and over to determine whether they respond differently from younger adult subjects [see Clinical Pharmacology (12.3)].

10 OVERDOSAGE

There is no specific treatment for NEMLUVIO overdosage. In the event of overdosage, contact Poison Control (1-800-222-1222) for the latest recommendations and monitor the patient for any signs or symptoms of adverse reactions and institute appropriate symptomatic treatment immediately.

11 DESCRIPTION

Nemolizumab-ilto, an interleukin-31 receptor alpha (IL-31RA) antagonist, is a humanized monoclonal modified immunoglobulin G (IgG) antibody with a molecular weight of approximately 144 kDa. Nemolizumab-ilto is produced by recombinant DNA technology in Chinese Hamster Ovary cells.

NEMLUVIO (nemolizumab-ilto) for injection is a sterile, preservative-free, white lyophilized powder in a dualchamber, single-dose, prefilled pen for subcutaneous use. One chamber contains 30 mg of nemolizumab-ilto with inactive ingredients arginine hydrochloride (9.5 mg), poloxamer 188 (0.15 mg), sucrose (25.8 mg), trometamol (0.10 mg), and tris hydrochloride for pH adjustment. The diluent, water for injection, is in the other chamber. Following reconstitution, each prefilled pen delivers 30 mg/0.49 mL of nemolizumab-ilto with a pH of 6.7 to 7.3.

12 CLINICAL PHARMACOLOGY

12.1 Mechanism of Action

Nemolizumab-ilto is a humanized IgG2 monoclonal antibody that inhibits IL-31 signaling by binding selectively to IL-31 RA. IL-31 is a naturally occurring cytokine that is involved in pruritus, inflammation, epidermal dysregulation, and fibrosis. Nemolizumab-ilto inhibited IL-31-induced responses including the release of proinflammatory cytokines and chemokines.

12.2 Pharmacodynamics

Pharmacodynamics of nemolizumab-ilto in the treatment of prurigo nodularis and atopic dermatitis are unknown.

12.3 Pharmacokinetics

After a single-dose, nemolizumab-ilto exposure increased dose proportionally over a dose range of 0.03 and 3 mg/kg following subcutaneous administration. After multiple doses, nemolizumab-ilto systemic exposure increased in an approximately dose-proportional manner across the subcutaneous dose range up to 30 mg. There was a decrease in bioavailability by 9% with the 60 mg subcutaneous dose and by 15% with the 90 mg subcutaneous dose.

- Prurigo Nodularis: Following multiple doses of NEMLUVIO in subjects with prurigo nodularis, the estimated mean (SD) steady-state trough concentrations of nemolizumab-ilto were 3.04 (1.23) μg/mL in subjects with bodyweight less than 90 kg; and 3.66 (1.63) μg/mL in subjects with bodyweight of 90 kg or more. Steady state nemolizumab-ilto concentrations were achieved by week 4 in subjects weighting less than 90 kg and by week 12 in subjects weighing 90 kg or more.
- Atopic Dermatitis: Following multiple doses of NEMLUVIO in subjects with atopic dermatitis, the estimated mean (SD) steady-state trough concentrations of nemolizumab-ilto were 2.63 (1.27) μg/mL for 30 mg administered every 4 weeks and 0.74 (0.44) μg/mL for 30 mg administered every 8 weeks. Steady-state nemolizumab-ilto concentrations were achieved 4 weeks after the initial 60 mg loading dose.

Absorption
Following an initial subcutaneous dose of 60 mg, nemolizumab-ilto reached peak mean (SD) concentrations (Cmax) of 7.5 (2.31) μg/mL by approximately 6 days post dose.

Distribution
The volume of distribution of nemolizumab-ilto was estimated to be 7.67 L.

Elimination
Nemolizumab-ilto is expected to be degraded in the same manner as endogenous IgG. The terminal elimination half-life (SD) of nemolizumab-ilto was estimated to be 18.9 (4.96) days and systemic clearance was estimated to be 0.263 L/day.

Metabolism
The metabolic pathway of nemolizumab-ilto has not been characterized. Nemolizumab-ilto is expected to be degraded into small peptides by catabolic pathways.

Specific Populations

Geriatric Populations

No clinically significant difference in the pharmacokinetics of nemolizumab-ilto was estimated based on age (subjects 18 to 65 years of age and older than 65 years of age). Dose adjustment in this population is not needed.

Pediatric Population

- Atopic Dermatitis: No clinically significant difference in the pharmacokinetics of nemolizumab-ilto was estimated in pediatric subjects 12 to 17 years of age compared to adults. Dose adjustment in this population is not needed.

Renal or Hepatic Impairment
No clinically significant differences in the pharmacokinetics of nemolizumab-ilto were estimated based on mild to moderate renal or hepatic impairments. The effect of severe renal and severe hepatic impairments on the pharmacokinetics of nemolizumab-ilto is unknown.

Body Weight
The exposure of nemolizumab-ilto decreases with increasing body weight. After a 30-mg dose every 4 weeks, the steady state mean exposure parameters (AUCss, Cmaxss and Ctrough) of subjects with bodyweight of above 87 kg is expected to be 1.7-fold lower than that of subjects weighing below 62 kg.

- Prurigo Nodularis: The variability in systemic exposure due to body weight had a clinically meaningful impact on skin lesion efficacy (IGA response) but not on pruritus improvement.
  Atopic Dermatitis: The difference in systemic exposure due to body weight had no clinically meaningful impact on efficacy in subjects with atopic dermatitis. Dose adjustment based on body weight is not needed.

Drug Interaction Studies
The effects of nemolizumab on the pharmacokinetics of midazolam (CYP3A4/5 substrate), warfarin (CYP2C9 substrate), omeprazole (CYP2C19 substrate), metoprolol (CYP2D6 substrate), and caffeine (CYP1A2 substrate) were evaluated in a study in 14 subjects with moderate to severe AD receiving an initial SC dose of 60 mg followed by 30 mg SC every four weeks for 12 weeks. No clinically significant changes in the exposure of CYP450 substrates before and after multiple nemolizumab injections were observed, with Cmax and AUC ratios ranging from 88.2 to 107.8%. The concomitant use of nemolizumab-ilto is unlikely to influence the PK profiles of CYP substrates.

12.6 Immunogenicity

The observed incidence of anti-drug antibodies is highly dependent on the sensitivity and specificity of the assay. Differences in assay methods preclude meaningful comparisons of the incidence of anti-drug antibodies in the studies described below with the incidence of anti-drug antibodies in other studies, including those of nemolizumab-ilto or other nemolizumab products.

Prurigo Nodularis:

- In the Phase 3 trials (OLYMPIA 1, OLYMPIA 2) up to 24 weeks, the incidence of treatment-emergent ADAs was 7%; neutralizing antibodies were seen in 3% of subjects.

Atopic Dermatitis:

- In the phase 3 trials (ARCADIA 1, ARCADIA 2) up to 16 weeks, the incidence of treatment-emergent ADAs was 6.1% (67/1092). Among subjects who continued treatment from week 16 through week 48 in the two studies, the ADA incidence was 13.9% (23/166) for those that received 30 mg every 4 weeks, and 10.6% (17/161) for those that received 30 mg every 8 weeks. Neutralizing antibody incidence was 4.5% (3/67) among the ADA+ subjects throughout 48 weeks in ARCADIA 1 and ARCADIA 2, respectively.

Anti-Drug Antibody Effects on Pharmacokinetics and Pharmacodynamics

- Prurigo Nodularis: In the phase 3 trials in subjects with prurigo nodularis, there was no identified clinically significant effect of anti-drug antibodies on the pharmacokinetics, safety or efficacy of nemolizumab-ilto over the treatment duration of 24 weeks.
- Atopic Dermatitis: In the phase 3 trials in subjects with atopic dermatitis, antibodies to nemolizumab-ilto were associated with reduced serum nemolizumab-ilto concentrations beyond Week 16. NEMLUVIO treated subjects who developed ADAs had nemolizumab-ilto concentrations that were 20% to 70% lower compared to subjects who did not develop ADAs. There was no clinically significant effect of anti-drug antibodies on safety or efficacy of nemolizumab-ilto over the treatment duration of 48 weeks.

13 NONCLINICAL TOXICOLOGY

13.1 Carcinogenesis, Mutagenesis, Impairment of Fertility

Animal studies have not been conducted to evaluate the carcinogenic or mutagenic potential of NEMLUVIO.
No effects on fertility parameters as reproductive organ morphology, menstrual cycle length, or sperm/testicular analysis were observed in male or female sexually mature cynomolgus monkeys that were administered nemolizumab-ilto at subcutaneous doses up to 25 mg/kg once every two weeks for 6 months (53 times the MRHD for PN and 72 times for AD, based on AUC comparison). The monkeys were not mated to evaluate fertility.

14 CLINICAL STUDIES

14.1 Prurigo Nodularis

Two randomized, double-blind, placebo-controlled trials (OLYMPIA 1 [NCT04501666] and OLYMPIA 2 [NCT04501679]) enrolled a total of 560 adult subjects with prurigo nodularis (PN). Disease severity was defined using an Investigator’s Global Assessment (IGA) in the overall assessment of prurigo nodularis nodules on a severity scale of 0 to 4. Subjects enrolled in these two trials had an IGA score ≥ 3, severe pruritus as defined by a weekly average of the peak pruritus numeric rating scale (PP-NRS) score of ≥7 on a scale of 0 to 10, and greater than or equal to 20 nodular lesions. OLYMPIA 1 and OLYMPIA 2 assessed the effect of NEMLUVIO on the signs and symptoms of PN, targeting improvement in skin lesions and pruritus over 16 weeks. In OLYMPIA 1, subjects were extended up to 24 weeks of treatment.

Subjects weighing less than 90 kg in the NEMLUVIO group received subcutaneous injections of NEMLUVIO 60 mg at Week 0, followed by NEMLUVIO 30 mg injections every 4 weeks. Subjects weighing 90 kg or more in the NEMLUVIO group received subcutaneous injections of NEMLUVIO 60 mg at Week 0 and every 4 weeks.

In these trials, at baseline, 60% of subjects were female, 81% were White, 9% were Asian, 7% were Black or African American; for ethnicity, 4% of subjects identified as Hispanic or Latino. Twenty-five (25)% of subjects were older than 65 years of age. Thirty-two (32)% of subjects had a history of atopy. The baseline weekly average PP-NRS score was a mean of 8.5. Fifty-eight (58)% of subjects had a baseline IGA score of 3 (moderate PN), and 42% of subjects had a baseline IGA of 4 (severe PN).

The PP-NRS score is a weekly average of daily PP-NRS scores on an 11-point scale from 0-10 that assesses the maximal intensity of pruritus in the last 24 hours with 0 being no itch and 10 being worst itch imaginable. The IGA is a 5-category scale, including “0 = clear”, “1 = almost clear”, “2 = mild”, “3 = moderate” or “4 = severe” indicating the investigator’s overall assessment of the pruriginous nodules.

Efficacy was assessed with the proportion of subjects with an improvement of ≥4 from baseline in PP-NRS, the proportion of subjects with an IGA of 0 (Clear) or 1 (Almost Clear) and a ≥2-point improvement from baseline, the proportion of subjects who achieved a response in both PP-NRS and IGA per the criteria described above, and the proportion of subjects with PP-NRS <2.

The efficacy results for OLYMPIA 1 and OLYMPIA 2 are presented in Table 3 and Figures 1, 2, and 3.

Table 3: Efficacy Results at Week 16 in Adult Subjects with PN in OLYMPIA1 and OLYMPIA 2
 | OLYMPIA 1 |  |  | OLYMPIA2
 | NEMLUVIO (N=190) | Placebo (N=96) | Difference from Placebo (95% CI) | NEMLUVIO (N=183) | Placebo (N=91) | Difference from Placebo (95% CI)
Proportion of subjects with both an improvement (reduction) of ≥4 from baseline in PP-NRS and IGA 0 or 1a,b | 22%a | 2%a | 15% (8%, 21%)a | 25%a | 4%a | 22% (14%, 30%)a
Proportion of subjects with IGA 0 or 1b | 26% | 7% | 15% (7%, 23%) | 38% | 11% | 29% (19%, 38%)
Proportion of subjects with an improvement (reduction) of ≥4 from baseline in PP-NRSb | 56% | 16% | 38% (27%, 48%) | 49% | 16% | 34% (23%, 45%)
Proportion of subjects with PP-NRS <2b | 32% | 4% | 28% (20%, 36%) | 31% | 7% | 26% (18%, 34%)
a Not adjusted for multiplicity.
b Subjects who received rescue therapy or had missing data (fewer than 4 PP-NRS daily diary entries in a 7-day period) were considered non-responders.

Figure 1: Proportion of Adult Subjects with PN with PP-NRS Improvement ≥4 from Baseline Over Time in OLYMPIA 1 and OLYMPIA 2a

a Subjects who received rescue therapy or had missing data (fewer than 4 PP-NRS daily diary entries in a 7-day period) were considered non-responders.

Figure 2: Proportion of Adult Subjects with PN with PP-NRS <2 Over Time in OLYMPIA 1 and OLYMPIA 2a

a Subjects who received rescue therapy or had missing data (fewer than 4 PP-NRS daily diary entries in a 7-day period) were considered non-responders.

Figure 3: Proportion of Adult Subjects with PN with IGA Responsea Over Time in OLYMPIA 1 and OLYMPA 2b

a Response was defined as an IGA of 0 (Clear) or 1 (Almost Clear) and a ≥2-point improvement from baseline.
b Subjects who received rescue therapy or had missing data were considered non-responders.

Examination of weight, age, gender, race, history of atopy, and prior treatment did not identify meaningful differences in response to NEMLUVIO among these subgroups at Week 16.

14.2 Atopic Dermatitis

Two randomized, double-blind, placebo-controlled trials (ARCADIA 1 [NCT03985943] and ARCADIA 2 [NCT03989349]) enrolled a total of 1728 subjects 12 years of age and older with moderate-to-severe atopic dermatitis not adequately controlled by topical treatments. Disease severity was defined by an Investigator’s Global Assessment (IGA) score of 3 (moderate) and 4 (severe) in the overall assessment of atopic dermatitis, an Eczema Area and Severity Index (EASI) score of ≥16, a minimum body surface area (BSA) involvement of ≥10%, and a Peak Pruritus Numeric Rating Scale (PP-NRS) score of ≥ 4.

During the initial 16-week treatment period, subjects in the NEMLUVIO group received an initial subcutaneous injection of NEMLUVIO 60 mg (two 30 mg injections), followed by 30 mg injections every 4 weeks. Concomitant low and/or medium potency TCS and/or TCI were administered for at least 14 days prior to baseline and continued during the trial. Based on disease activity, these concomitant therapies could be tapered and/or discontinued at investigator discretion.

After 16 weeks, subjects achieving either EASI-75 or IGA success (i.e. NEMLUVIO responders) continued into the trial maintenance period for another 32 weeks to evaluate the maintenance of response achieved at Week 16. NEMLUVIO responders were re-randomized to receive either NEMLUVIO 30 mg every 4 weeks, NEMLUVIO 30 mg every 8 weeks, or placebo every 4 weeks (all groups continued background TCS/TCI). Subjects randomized to placebo in the initial treatment period who achieved the same clinical response at Week 16 continued to receive placebo every 4 weeks.

In these trials, at baseline, 51% of subjects were male, 80% were White, 13% were Asian, and 6% were Black or African American; for ethnicity, 9% of subjects identified as Hispanic or Latino. Fifteen (15)% of subjects were 12-17 years of age. Seventy (70)% of subjects had a baseline IGA score of 3 (moderate AD), and 30% of subjects had a baseline IGA score of 4 (severe AD). The baseline mean EASI score was 27.5 and the baseline mean weekly average PP-NRS was 7.1. Overall, 63% of subjects received other previous systemic treatments for AD.

The IGA is a 5-category scale, including “0 = clear”, “1 = almost clear”, “2 = mild”, “3 = moderate” or “4 = severe” indicating the investigator’s overall assessment of the AD. EASI scores range from 0 to 72 points and reflect the severity and extent of AD. EASI-75 indicates at least a 75% improvement in EASI score from baseline. The PP-NRS score is a weekly average of daily PP NRS scores on an 11-point scale from 0-10 that assesses the maximal intensity of pruritus in the last 24 hours with 0 being no itch and 10 being worst itch imaginable.

Both ARCADIA 1 and ARCADIA 2 assessed the co-primary endpoints of:

- Proportion of subjects with an IGA success (defined as an IGA of 0 [clear] or 1 [almost clear] and a ≥2- point reduction from baseline) at Week 16
- Proportion of subjects with EASI-75 (≥75% improvement in EASI from baseline) at Week 16

PP-NRS improvement ≥ 4 from baseline at Week 16 was a key secondary outcome in both trials.

Clinical Response at Week 16 (ARCADIA 1 and ARCADIA 2)
The efficacy results for ARCADIA 1 and ARCADIA 2 evaluating the initial treatment period with NEMLUVIO administered every 4 weeks over 16 weeks are presented in Table 4.

Table 4. Efficacy Results of NEMLUVIO (Every 4 Weeks) with Concomitant TCS/TCI at Week 16 in Adult and Pediatric Subjects 12 Years of Age and Older with Moderate to Severe AD in ARCADIA 1 and ARCADIA 2
 | ARCADIA 1 |  |  | ARCADIA 2
 | NEMLU VIO Every 4 Weeks + TCS/TCI | Placebo + TCS/TCI | Difference from Placebo (95% CI) | NEMLUVIO Every 4 Weeks + TCS/TCI | Placebo + TCS/TCI | Difference from Placebo (95% CI)
Number of subjects randomized | 620 | 321 |  | 522 | 265
Proportion of subjects with IGA 0 or 1a | 36% | 25% | 12% (6%, 17%) | 38% | 26% | 12% (6%, 19%)
Proportion of subjects with EASI-75a | 44% | 29% | 15% (9%, 21%) | 42% | 30% | 12% (6%, 19%)
Proportion of subjects with an improvement (reduction) of ≥4 from baseline in PP-NRSa | 33% | 15% | 18% (13%, 23%) | 36% | 15% | 21% (15%, 27%)
a Subjects who received rescue treatment or had missing data (fewer than 4 PP-NRS daily diary entries in a 7-day period) were considered non-responders.

Examination of weight, age, gender, race, and prior treatment did not identify meaningful difference in response to NEMLUVIO among these subgroups at Week 16.

Maintenance and Durability of Response (Week 16 to Week 48)
The maintenance and durability of response in NEMLUVIO responders (IGA 0/1 or EASI-75 at Week 16) was evaluated between Week 16 and Week 48 in ARCADIA 1 and ARCADIA 2 trials. For the maintenance treatment period, NEMLUVIO responders were re-randomized to NEMLUVIO 30 mg every 4 weeks, NEMLUVIO 30 mg every 8 weeks or placebo every 4 weeks (NEMLUVIO withdrawal) with concomitant TCS/TCI. The results are presented in Table 5.

Table 5. Efficacy Results of NEMLUVIO with Concomitant TCS/TCI at Week 48 in Adult and Pediatric Subjects 12 Years of Age and Older with Moderate to Severe AD in ARCADIA 1 and ARCADIA 2
 | NEMLUVIO Every 4 Weeks + TCS/TCI | NEMLUVIO Every 8 Weeks + TCS/TCI | Placebo + TCS/TCI
Number of subjects who were IGA Respondersa at Week 16 | 142 | 142 | 131
Proportion of subjects with IGA 0 or 1b at Week 48 | 63% | 64% | 55%
Number of subjects who were EASI-75 Responders at Week 16 | 163 | 163 | 157
Proportion of subjects with EASI-75b at Week 48 | 75% | 77% | 65%
a Responder was defined as a subject with an IGA of 0 (clear) or 1 (almost clear) and a ≥ 2-point reduction from baseline.
b Subjects who received rescue treatment or with missing data were considered non-responders.

16 HOW SUPPLIED/STORAGE AND HANDLING

How Supplied
NEMLUVIO (nemolizumab-ilto) for injection is a sterile, preservative-free, white lyophilized powder available in a single-dose, dual-chamber, prefilled pen containing 30 mg of nemolizumab-ilto in one chamber and the diluent, water for injection, in the other chamber. Following reconstitution, each prefilled pen delivers 30 mg/0.49 mL of nemolizumab-ilto.

Each carton contains 1 single-dose prefilled pen:

Presentation | Pack size | NDC#
Prefilled Pen | Pack of 1 pen | 0299-6220-15

Storage and Handling
Store the NEMLUVIO dual-chamber, prefilled pen in a refrigerator at 36°F to 46°F (2°C to 8°C) in the original carton to protect from light until the expiration date. Do not freeze. Do NOT expose to heat or direct sunlight.

Alternatively, the NEMLUVIO carton containing the unused dual-chamber, prefilled pen may be stored at room temperature [up to 77°F (25°C)] for up to 90 days. Write the date the NEMLUVIO dual-chamber, prefilled pen is first removed from the refrigerator in the space provided on the inner partition for the pen. Do not use the NEMLUVIO dual-chamber, prefilled pen beyond the expiration date or 90 days after the date it was first removed from the refrigerator (whichever is earlier).

17 PATIENT COUNSELING INFORMATION

Advise the patient to read the FDA-approved patient labeling (Patient Information and Instructions for Use).

Hypersensitivity
Advise patients to seek immediate medical attention and discontinue NEMLUVIO if they experience any symptoms of hypersensitivity reactions [see Warnings and Precautions (5.1)].
Vaccinations
Instruct patients to inform their healthcare provider that they are taking NEMLUVIO prior to a potential vaccination [see Warnings and Precautions (5.2)].
Administration Instructions:

- Instruct patients and/or caregivers to receive proper training in subcutaneous injection technique prior to self-injection [see Dosage and Administration (2.5)]. Inform patients and/or caregivers that Galderma Customer Support may be called toll-free for assistance at 1-866-735-4137.
- Inform patients that NEMLUVIO must be reconstituted prior to administration. Advise patients and/or caregivers to refer to the Instructions for Use that accompanies the NEMLUVIO pen for complete mixing and administration instructions with illustrations [see Dosage and Administration (2.5, 2.6), Instructions for Use].
- Inform patients and/or caregivers of proper pen disposal and caution against any reuse of needles. Instruct patients and/or caregivers to discard used pens in an appropriate sharps disposal container following safe needle disposal practices[see Instructions for Use].
- Advise patients and/or caregivers of the importance of complying with dosing schedule. If a dose is missed, instruct patients and/or caregivers to administer the injection as soon as possible, and thereafter, resume dosing at the regular scheduled time [see Dosage and Administration (2.4)].

Manufactured by:
Galderma Laboratories, L.P., Dallas, TX 75201
U.S. License No. 2289
NEMLUVIO® is a registered trademark of Galderma.
© 2025 Galderma Laboratories, L.P. All rights reserved.

PATIENT INFORMATION
NEMLUVIO® [Nem LOO vee oh]
(nemolizumab-ilto)
for injection, for subcutaneous use

What is NEMLUVIO?

NEMLUVIO is a prescription medicine used:

- to treat adults with prurigo nodularis.
- to treat adults and children 12 years of age and older with moderate-to-severe eczema (atopic dermatitis) that is not well controlled with prescription therapies used on the skin (topical). NEMLUVIO can be used with certain prescription topical medicines.

It is not known if NEMLUVIO is safe and effective in children with prurigo nodularis under 18 years of age.
It is not known if NEMLUVIO is safe and effective in children with atopic dermatitis under 12 years of age.

Do not take NEMLUVIO if you are allergic to nemolizumab-ilto or to any ingredients in NEMLUVIO. See the end of this Patient Information leaflet for a complete list of ingredients in NEMLUVIO.

Before taking NEMLUVIO, tell your healthcare provider about all of your medical conditions, including if you:

- are scheduled to receive any vaccination. You should avoid receiving a live vaccine right before or during treatment with NEMLUVIO.
- are pregnant or plan to become pregnant. It is not known whether NEMLUVIO will harm your unborn baby.
- are breastfeeding or plan to breastfeed. It is not known whether NEMLUVIO passes into your breast milk and if it can harm your baby.

Tell your healthcare provider about all of the medicines you take, including prescription and over-the-counter medicines, vitamins, and herbal supplements.

How should I take NEMLUVIO?

- See the detailed Instructions for Use that comes with NEMLUVIO for information on how to prepare and inject NEMLUVIO and how to properly store and throw away (dispose of) used NEMLUVIO prefilled pens.
- Use NEMLUVIO exactly as prescribed by your healthcare provider.
- Use NEMLUVIO with prescription topical therapies. When your eczema has sufficiently improved, your healthcare provider may discontinue topical therapies.
- Your healthcare provider will tell you how much NEMLUVIO to inject and how often to inject it.
- NEMLUVIO comes as a single-dose prefilled pen with a needle guard.
- NEMLUVIO is given as an injection under the skin (subcutaneous injection).
- If your healthcare provider decides that you or a caregiver can give the injections of NEMLUVIO, you or your caregiver should receive training on the right way to prepare and inject NEMLUVIO. Do not try to inject NEMLUVIO until you have been shown the right way by your healthcare provider.
- If you miss a dose, inject the missed dose as soon as possible, then continue with your next dose at your regular scheduled time.
- If you inject too much NEMLUVIO, call your healthcare provider or the Poison Help line at 1-800-222-1222 or go to the nearest hospital emergency room right away.
- Your healthcare provider may prescribe other medicines to use with NEMLUVIO. Use the other prescribed medicines exactly as your healthcare provider tells you to.

What should I avoid while taking NEMLUVIO?
You should avoid receiving live vaccines while taking NEMLUVIO.

What are the possible side effects of NEMLUVIO?
NEMLUVIO may cause serious side effects, including:

- allergic reactions (hypersensitivity). NEMLUVIO can cause allergic reactions that can sometimes be serious. Stop using NEMLUVIO and tell your healthcare provider or get emergency help right away if you get any of the following symptoms:

o breathing problems
or wheezing

o swelling of the face, lips, mouth, tongue, or throat

o fainting, dizziness, feeling lightheaded

o fast pulse

o swollen lymph nodes

o joint pain

o fever

o skin rash (red or rough skin)

o nausea or vomiting

o general ill feeling

o cramps in your stomach area

The most common side effects of NEMLUVIO in people treated for prurigo nodularis include:

- headache
- skin rashes: atopic dermatitis (a type of eczema), eczema, and eczema nummular (scattered circular patches)

The most common side effects of NEMLUVIO in people treated for atopic dermatitis include:

- headache
- joint pain
- hives (itchy red rash or wheals)
- muscle aches

These are not all of the possible side effects of NEMLUVIO.
Call your doctor for medical advice about side effects. You may report side effects to FDA at 1-800-FDA-1088.

How should I store NEMLUVIO?

- Store NEMLUVIO in the refrigerator between 36°F to 46°F (2°C to 8°C) until the expiration date.
- Store NEMLUVIO in the original carton to protect from light.
- NEMLUVIO can be stored at room temperature up to 77ºF (25ºC) for a single period up to 90 days.
- Throw away (dispose of) NEMLUVIO after the expiration date and any NEMLUVIO that has been left at room temperature for longer than 90 days.
- After the NEMLUVIO lyophilized powder and water for injection are mixed (reconstituted), NEMLUVIO must be used within 4 hours or thrown away (discarded).
- Do not heat or put NEMLUVIO pen into direct sunlight.
- Do not freeze the NEMLUVIO pen.
- If the NEMLUVIO pen was heated or frozen, throw it away (dispose of it).

Keep NEMLUVIO and all medicines out of the reach of children.

General information about the safe and effective use of NEMLUVIO.
Medicines are sometimes prescribed for purposes other than those listed in a Patient Information leaflet. Do not use NEMLUVIO for a condition for which it was not prescribed. Do not give NEMLUVIO to other people, even if they have the same symptoms that you have. It may harm them. You can ask your pharmacist or healthcare provider for information about NEMLUVIO that is written for healthcare professionals.

What are the ingredients in NEMLUVIO?
Active ingredient: nemolizumab-ilto
Inactive ingredients: arginine hydrochloride, poloxamer 188, sucrose, trometamol, and tris hydrochloride.

Manufactured by: Galderma Laboratories, L.P., Dallas, TX 75201
U.S. License No. 2289
NEMLUVIO® is a registered trademark of Galderma.
© 2025 Galderma Laboratories, L.P. All rights reserved.
For more information, go to www.NEMLUVIO.com or call 1-866-735-4137.

This Patient Information has been approved by the U.S. Food and Drug Administration.
Revised: 06/2025

INSTRUCTIONS FOR USE

NEMLUVIO® [Nem LOO vee oh]
(nemolizumab-ilto)
for injection, for subcutaneous use

This Instructions for Use contains information on how to inject NEMLUVIO.
Read and understand these instructions before using the NEMLUVIO pen.
Do not inject yourself or someone else until you have been instructed how to inject NEMLUVIO.
In adolescents (ages 12 to 17 years old), it is recommended that NEMLUVIO be given by or under supervision of a trained adult or caregiver.
Your healthcare provider will instruct you or your caregiver how to prepare and inject a dose of NEMLUVIO before you try to do it yourself the first time. Call your healthcare provider if you have any questions.
NEMLUVIO is supplied as a single-dose pen (called NEMLUVIO pen or pen in these instructions). It contains medicine (30 mg of lyophilized powder) in one chamber and water for dissolving the medicine in the other chamber. Before you can inject it, you must mix the lyophilized powder with the water for dissolving the medicine.

Important Information
What you need to know before using the NEMLUVIO pen:

- Read all the instructions carefully before using the NEMLUVIO pen.
- Mark your calendar ahead of time to remember when to take NEMLUVIO.
- Do not use the NEMLUVIO pen if it has been dropped on a hard surface or is damaged, cracked or broken.
- Follow all steps exactly as described. This makes sure that you get the correct dose of medicine.
- Make sure that the lyophilized powder is completely dissolved before injecting (Step 9). After dissolving the powder, inject the medicine right away to avoid any contamination or break down of medicine (degradation).
- To use the pen for injection, while holding upright, gently twist (do not pull) the gray cap to the left (counterclockwise) until the orange needle guard pops up. Then, gently pull the gray cap off the orange needle guard. Do not press the orange needle guard until ready to inject (Step 12).
- In some cases, your healthcare provider may prescribe 2 pens for a full dose. Use the second NEMLUVIO pen right away after using the first pen. Choose a different injection site at least 1 inch away from the first injection site.
- To reduce the risk of accidental needle stick injury, each NEMLUVIO pen has an orange needle guard. After injecting the medicine and lifting the pen from your skin, the orange needle guard locks into place automatically to cover the needle (Step 16).
- Throw away (dispose of) the used NEMLUVIO pen right away after use in a sharps disposal container. See Section C: Throwing away (Disposing of) NEMLUVIO below.

Storage Information:

- Store the NEMLUVIO pen in the refrigerator between 36°F to 46°F (2°C to 8°C) until the expiration date.
- Store the NEMLUVIO pen in the original carton to protect it from light.
- The NEMLUVIO pen can be stored at room temperature up to 77°F (25°C) for up to 90 days.
- Throw away (dispose of) the NEMLUVIO pen after the expiration date and any NEMLUVIO pen that has been left at room temperature longer than 90 days.
- After the NEMLUVIO pen lyophilized powder and water for injection are mixed (reconstituted), the NEMLUVIO pen must be used within 4 hours or thrown away (disposed of).
- Do not heat or put the NEMLUVIO pen into direct sunlight.
- Do not freeze the NEMLUVIO pen.
- If the NEMLUVIO pen was heated or frozen, throw it away (dispose of it).

Keep the NEMLUVIO pen and all medicines out of the reach of children.

Traveling Information:

- Generally, you are allowed to carry pens with you on an airplane. Be sure to carry the NEMLUVIO pens in the original carton with you in your carry-on luggage.
  If you have any other questions refer to the Frequently asked questions (FAQs) on the back of this leaflet.

A. Preparing to inject NEMLUVIO

Step 1: Let NEMLUVIO reach room temperature
Injecting cold medicine might result in pain at the injection site.
Take the NEMLUVIO carton out of the refrigerator and let it come to room temperature for 30 to 45 minutes before starting Step 2 (see Figure A).

Do not:

- warm the pen with any heat source (such as microwave or direct sunlight). This might damage NEMLUVIO.
- directly expose the pen to liquids.

Step 2: Wash your hands
a. Wash your hands with soap and water to avoid contamination and infection (see Figure B).
b. Dry hands completely.

Step 3: Gather Supplies (see Figure C)
a. Remove the pen from the carton.
b. Gather the following supplies on a clean, flat and well-lit surface:

1. Pen
2. Alcohol wipes*
3. Sharps disposal container*
4. Gauze pads or cotton balls*

*Items not included in the carton.
Note: In some cases, your healthcare provider may prescribe 2 pens. Use 1 pen after the other.

Step 4: Check the NEMLUVIO pen for the following:
a. Expiration date has not passed.
b. The lyophilized powder is white and not dissolved (see Figure D).
c. The pen has not been dropped and is not damaged or cracked.
Do not use the pen, unless all conditions above are met.
If any condition is not met, call: 1-866-735-4137.
Throw away (dispose of) the pen and use a new one (see Section C: Throwing away (Disposing of) NEMLUVIO).

Step 5: Activate the NEMLUVIO pen
Hold the pen upright and unlock the pen by turning the activation knob to the right until it stops (see Figure E).
This starts the process of transferring water to the powder chamber.
Only turn the activation knob to the right once.

Step 6: Wait until the gray rod stops moving
Watch inspection window until gray rod has stopped moving (see Figure F).
Do not shake the pen. Shaking the pen before the gray rod has completely stopped can affect the medicine dose.

Step 7: Dissolve the medicine
When the gray rod has completely stopped, hold the pen upright and shake the pen up and down for 30 seconds (see Figure G).

Step 8: Wait 5 minutes for bubbles to decrease
Wait for bubbles to decrease and the lyophilized powder to dissolve completely. This will take about 5 minutes (see Figure H).
Note: If the medicine has not dissolved completely, shake the pen up and down again for 30 seconds and then wait 5 minutes.
Note: It is normal for a small foam layer or a few small air bubbles to remain in the dissolved medicine.

Step 9: Check the medicine in the inspection window
Check to see if the dissolved medicine:

1. is clear and colorless to slightly yellow,
2. does not contain particles (see Figure I).

Do not use the pen if the dissolved medicine is cloudy or contains any particles.
Throw away (dispose of) the pen and use a new one (see Section C: Throwing away (Disposing of) NEMLUVIO).
Note: After the medicine has dissolved, it must be used within 4 hours. During this time, it should be kept at room temperature (up to 77°F (25°C)). If you have not used it within 4 hours, throw it away (dispose of it).

B. Injecting NEMLUVIO

Step 10: Select one injection site (see Figure J)
Note: When using a second pen, select a different injection site at least 1 inch away from the first injection site.
Select the injection site using the following chart:

Where not to inject:

- near your waistline within about 2 inches around the navel.
- into tender, bruised, red skin, or areas with scars or stretch marks.
- twice into the same site (for example, within 1 inch).

Step 11: Clean the injection site (see Figure K)
a. Always use a new alcohol wipe to clean the injection site to avoid contamination and infection.
b. Let the skin air dry.

Do not:

- touch the injection site after cleaning.
- fan, or blow air on the cleaned injection site.
- reuse the alcohol wipe.

Step 12: Twist the gray cap
Do not:

- pull the gray cap when twisting to avoid damaging the device.
- touch the orange needle guard.

1. Hold the pen upright (see Figure L, a)
2. Gently twist the gray cap to the left (counterclockwise) until the orange needle guard pops up (see Figure L, b).
3. Gently pull the gray cap off the orange needle guard (see Figure L, c). Do not press on the orange needle guard until ready to inject.
4. After cap removal, please throw away (dispose of) the cap in a sharps disposal container (see Step 17).

Note: If the cap cannot be removed, refer back to Step 5 and make sure the activation knob is turned completely to the right until it stops.

Step 13: Place the NEMLUVIO pen

Read Steps 13-16 before starting Step 13.

Note: Always inject the way your healthcare provider showed you.
Place the pen on the injection site vertically so that the orange needle guard is flat against the skin (see Figure M).
Note: Make sure you can easily see the inspection window during injection.

Step 14: Start injection and hold the NEMLUVIO pen on the skin
Gently push the pen down until the orange needle guard is completely pushed in.
The injection starts right away with a click (see Figure N).
The orange rod will begin to move down the injection window.
Do not lift the pen yet and keep pushing down.

Step 15: Inject for 15 seconds
Hold the pen in position and slowly count to 15 or use a timer or clock to count 15 seconds.
Check the inspection window to make sure the orange rod and gray rod have stopped moving (see Figure O).
This means the injection has been completed.
Note: It is normal that the orange rod does not cover the whole inspection window at the end of injection.
Do not lift the pen until the orange rod and gray rod have stopped moving.
If the orange rod is not visible, please call: 1-866-735-4137. Throw away (dispose of) the pen and use a new one (see Section C for disposal details).

Step 16: Lift the NEMLUVIO pen up
a. Lift the pen straight up from your skin.
The orange needle guard automatically locks into place to cover the needle (see Figure P).
b. If there is bleeding, press a cotton ball or gauze over the injection site.
Do not rub the injection site.

C. Throwing away (disposing of) NEMLUVIO

Step 17: Throw away (dispose of) NEMLUVIO in a sharps disposal container
Avoid contact with the needle.
Throw away (dispose of) the used pen and the gray cap in an FDA cleared sharps disposal container right away after use (see Figure Q).
Do not:

- recap the pen after use,
- dispose of the NEMLUVIO pen and cap in your household trash,
- dispose of your used sharps disposal container in your household trash unless your community guidelines permit this,
- recycle your used sharps disposal container.

If you do not have an FDA-cleared sharps disposal container, you may use a household container that is:

- made of a heavy-duty plastic,
- can be closed with a tight-fitting, puncture-resistant lid, without sharps being able to come out,
- upright and stable during use,
- leak-resistant and
- properly labeled to warn of hazardous waste inside the container.

When your sharps disposal container is almost full, you will need to follow your community guidelines for the right way to dispose of your sharps disposal container.
There may be state or local laws about how you should dispose of used pens.

For more information about safe sharps disposal, and for specific information about sharps disposal in the state that you live in, go to the FDA’s website at:
http://www.fda.gov/safesharpsdisposal

FAQs (Frequently asked questions)

Needle |  | Injecting the medicine
Where is the needle? |  | Why do I need to hold the pen upright while removing the gray cap?
The needle is attached to the NEMLUVIO pen and covered by the gray cap. When you twist the gray cap, the orange needle guard pops up and covers the needle until you inject the medicine. For more information, please see the figures in Step 12 in this Instructions for Use. |  | Holding the NEMLUVIO pen with the gray cap upright helps prevent the medicine from leaking. It is normal to see a few drops of medicine inside the gray cap even when you hold the pen upright and remove the gray cap.
Dissolving the medicine |  | How do I know I injected myself the full dose of medicine in the pen?
How do I know if the medicine is fully dissolved? |  | To be sure you get the full dose of medicine, press and hold the NEMLUVIO pen against your skin. You will feel the needle go into your skin. Hold the NEMLUVIO pen against your skin for 15 seconds. This will allow enough time for all the medicine to go from the pen to under your skin. Only remove the NEMLUVIO pen when the orange rod and the gray rod have stopped moving. After removing the NEMLUVIO pen, look for the orange rod in the window as a way to tell that the dose has been given. If the orange rod does not appear, contact 1-866-735-4137. For details please refer to Step 15 in this Instructions for Use.
To dissolve, shake the NEMLUVIO pen in an upright position, up and down, until the white particles are no longer on the bottom, top, or sides. The dissolved medicine should look clear. Please refer to Step 9 in this Instructions for Use. After shaking the NEMLUVIO pen, look through both sides of the inspection window. You should not see any white particles along the bottom, top, or sides. It is acceptable to have small air bubbles or a small foam layer on top of the medicine. It does not harm you. If you see white particles in the medicine, the medicine powder is not fully dissolved. |  | To be sure you get the full dose of medicine, press and hold the NEMLUVIO pen against your skin. You will feel the needle go into your skin. Hold the NEMLUVIO pen against your skin for 15 seconds. This will allow enough time for all the medicine to go from the pen to under your skin. Only remove the NEMLUVIO pen when the orange rod and the gray rod have stopped moving. After removing the NEMLUVIO pen, look for the orange rod in the window as a way to tell that the dose has been given. If the orange rod does not appear, contact 1-866-735-4137. For details please refer to Step 15 in this Instructions for Use.
Storage |  | General Information
How should I store the NEMLUVIO pen? |  | Is it necessary to receive instructions on how to use the NEMLUVIO pen from a healthcare provider?
The NEMLUVIO pen should be stored in the refrigerator in its original carton to protect it from light. It can be stored at room temperature for up to 77°F (25°C) for a single period up to 90 days. The device should not come in contact with liquids. |  | Yes. Do not inject the medicine if you did not receive a demonstration by your healthcare provider. You should contact your healthcare provider right away to receive the information and instructions on how to use the NEMLUVIO pen.
Where do I find the expiration date? |  | Where can I get more information about using NEMLUVIO:
You can find the expiration date on the NEMLUVIO pen labeled as EXP YYYY-MM. Do not use the NEMLUVIO pen past the expiration date. |  | If you have other questions about how to use the NEMLUVIO pen: - Call your healthcare provider - Call 1-866-735-4137
What should I do if the medicine has been frozen?
Do not use the NEMLUVIO pen if it has been frozen. Throw away (dispose of) the NEMLUVIO pen and use a new one.

Manufactured by:
Galderma Laboratories, L.P.
Dallas, TX 75201
This Instructions for Use has been approved by the U.S. Food and Drug Administration
U.S. License No. 2289
Issued: 06/2025

PRINCIPAL DISPLAY PANEL 30 mg PRE-FILLED DUAL-CHAMBER PEN CARTON

IMPORTANT:
CAREFULLY read and follow Instructions for Use.
This pen requires specific steps before injection.
1 Single-Dose Pre-Filled Dual-Chamber Pen
Keep out of reach of children. Do NOT use after expiration.
Do NOT use if seal is broken or damaged. Dosage: See Prescribing
For Subcutaneous Use
MUST BE RECONSTITUTED BEFORE INJECTION
Single-Dose only
GALDERMA
NDC 0299-6220-15 Rx only
nemluvio™
(nemluvio-ilto) for injection 30 mg